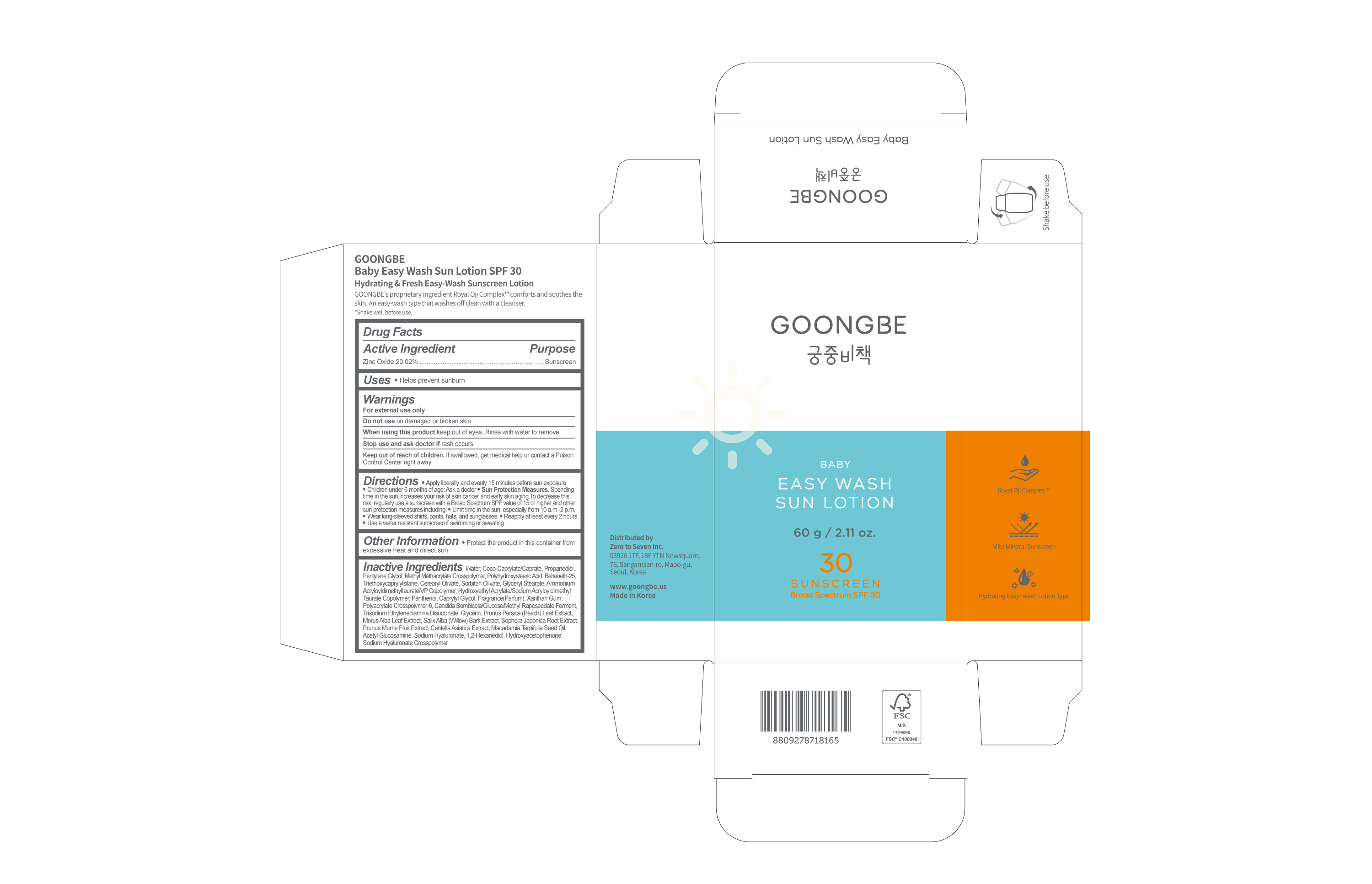 DRUG LABEL: GOONGBE Baby Easy Wash SunLotion SPF 30
NDC: 43319-071 | Form: LOTION
Manufacturer: Zero to Seven Inc.
Category: otc | Type: HUMAN OTC DRUG LABEL
Date: 20241118

ACTIVE INGREDIENTS: ZINC OXIDE 20.026 g/100 g
INACTIVE INGREDIENTS: PENTYLENE GLYCOL; COCO-CAPRYLATE/CAPRATE; PROPANEDIOL; WATER

Dosage & Administration

Dosage form: Lotion

Administration: Topical

Warnings

For external use only

Do not use on damaged or broken skin.

When using this product keep out of eyes.

Rinse with water to remove Stop use and ask doctor if rash occurs

Keep out of reach of children. If swallowed, get medical help or contact a Poison Control Center right away

Inactive Ingredients

Water, Coco-Caprylate/Caprate, Propanediol, Pentylene Glycol, Methyl Methacrylate Crosspolymer, Polyhydroxystearic Acid, Beheneth-25, Triethoxycaprylylsilane, Cetearyl Olivate, Sorbitan Olivate, Glyceryl Stearate, Ammonium Acryloyldimethyltaurate/VP Copolymer, Hydroxyethyl Acrylate/Sodium Acryloyldimethyl Taurate Copolymer, Panthenol, Caprylyl Glycol, Fragrance(Parfum), Xanthan Gum, Polyacrylate Crosspolymer-6, Candida Bombicola/Glucose/Methyl Rapeseedate Ferment, Trisodium Ethylenediamine Disuccinate, Glycerin, Prunus Persica (Peach) Leaf Extract, Morus Alba Leaf Extract, Salix Alba (Willow) Bark Extract, Sophora Japonica Root Extract, Prunus Mume Fruit Extract, Centella Asiatica Extract, Macadamia Ternifolia Seed Oil, Acetyl Glucosamine, Sodium Hyaluronate, 1,2-Hexanediol, Hydroxyacetophenone, Sodium Hyaluronate Crosspolymer

Usage

Helps prevent sunburn

Keep out of reach of children.

If swallowed, get medical help or contact a Poison Control Center right away.

Purpose

sunscreen